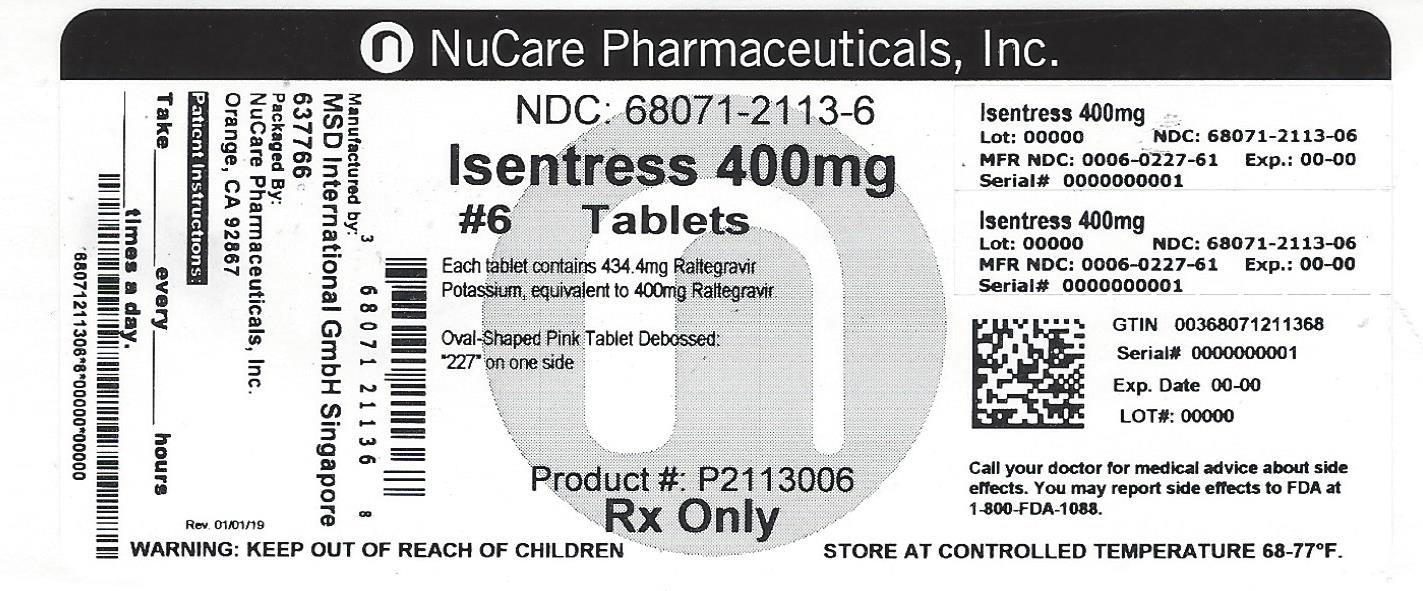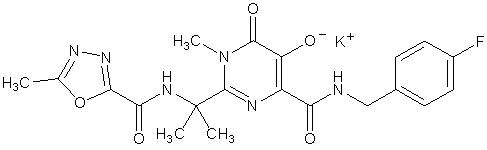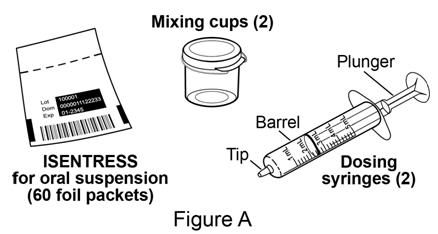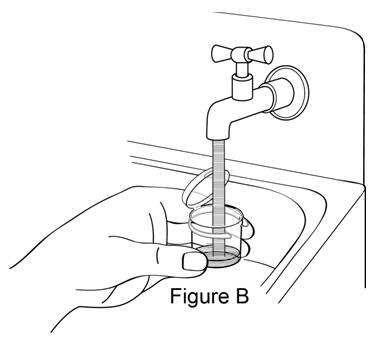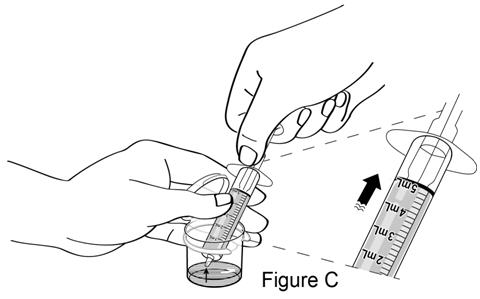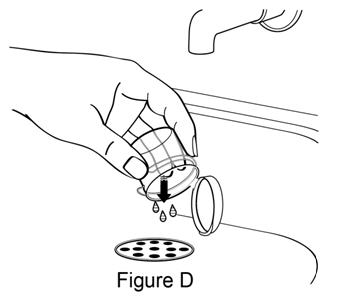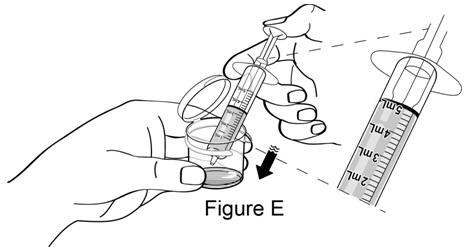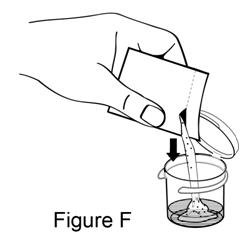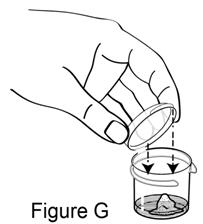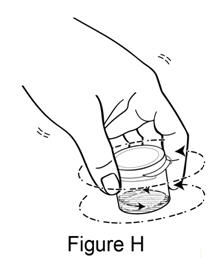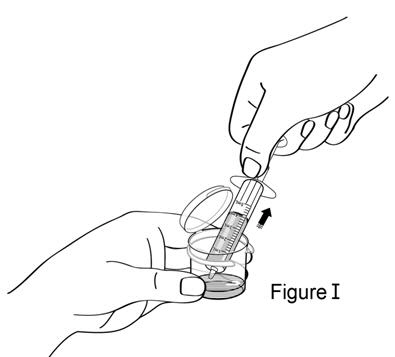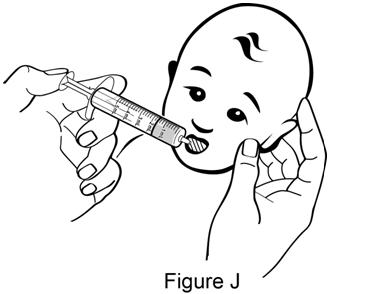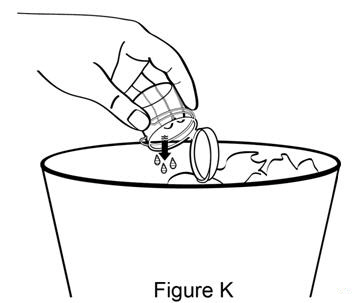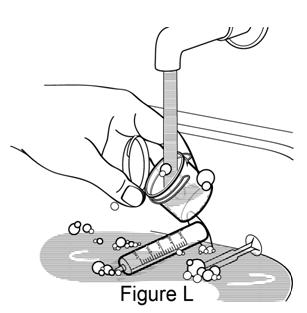 DRUG LABEL: ISENTRESS
NDC: 68071-2113 | Form: TABLET, FILM COATED
Manufacturer: NuCare Pharmaceuticals,Inc.
Category: prescription | Type: HUMAN PRESCRIPTION DRUG LABEL
Date: 20240717

ACTIVE INGREDIENTS: RALTEGRAVIR POTASSIUM 400 mg/1 1
INACTIVE INGREDIENTS: FERROSOFERRIC OXIDE; BUTYLATED HYDROXYTOLUENE; CALCIUM PHOSPHATE, DIBASIC, ANHYDROUS; HYPROMELLOSES; LACTOSE MONOHYDRATE; MAGNESIUM STEARATE; CELLULOSE, MICROCRYSTALLINE; POLOXAMER 407; POLYETHYLENE GLYCOL 3350; POLYVINYL ALCOHOL; FERRIC OXIDE RED; SODIUM STEARYL FUMARATE; TALC; TITANIUM DIOXIDE

HIGHLIGHTS OF PRESCRIBING INFORMATION

These highlights do not include all the information needed to use ISENTRESS safely and effectively. See full prescribing information for ISENTRESS.
ISENTRESS® (raltegravir) film-coated tablets, for oral use
ISENTRESS® (raltegravir) chewable tablets, for oral use
ISENTRESS® (raltegravir) for oral suspension
Initial U.S. Approval: 2007

1 INDICATIONS AND USAGE

ISENTRESS is a human immunodeficiency virus integrase strand transfer inhibitor (HIV-1 INSTI) indicated:

- In combination with other antiretroviral agents for the treatment of HIV-1 infection in patients 4 weeks of age and older (1).

The use of other active agents with ISENTRESS is associated with a greater likelihood of treatment response (14).

2 DOSAGE AND ADMINISTRATION

ISENTRESS can be administered with or without food (2.1).

Do not substitute ISENTRESS chewable tablets or ISENTRESS for oral suspension for the ISENTRESS 400 mg film-coated tablet.

See specific dosing guidance for chewable tablets and the formulation for oral suspension (2.1).

Adults

- 400 mg film-coated tablet orally, twice daily (2.2).
- During coadministration with rifampin in adults, 800 mg twice daily (2.1).

Children and Adolescents

- If at least 25 kg: One 400 mg film-coated tablet orally, twice daily. If unable to swallow a tablet, consider the chewable tablet, as specified in Table 1 (2.3).
- If at least 3 kg to less than 25 kg: Weight based dosing, as specified in Table 2. For patients weighing between 11 and 20 kg, either the chewable tablet or the formulation for oral suspension can be used, as specified in Table 2 (2.3).

3 DOSAGE FORMS AND STRENGTHS

- Film-Coated Tablets: 400 mg (3).
- Chewable Tablets: 100 mg scored and 25 mg (3).
- For Oral Suspension: Single-use packet of 100 mg (3).

4 CONTRAINDICATIONS

None (4).

5 WARNINGS AND PRECAUTIONS

- Severe, potentially life-threatening and fatal skin reactions have been reported. This includes cases of Stevens-Johnson syndrome, hypersensitivity reaction and toxic epidermal necrolysis. Immediately discontinue treatment with ISENTRESS and other suspect agents if severe hypersensitivity, severe rash, or rash with systemic symptoms or liver aminotransferase elevations develops and monitor clinical status, including liver aminotransferases closely (5.1).
- Monitor for Immune Reconstitution Syndrome (5.2).
- Inform patients with phenylketonuria that the 100 mg and 25 mg chewable tablets contain phenylalanine (5.3).

6 ADVERSE REACTIONS

- The most common adverse reactions of moderate to severe intensity (≥2%) are insomnia, headache, dizziness, nausea and fatigue (6.1).
- Creatine kinase elevations were observed in subjects who received ISENTRESS. Myopathy and rhabdomyolysis have been reported. Use with caution in patients at increased risk of myopathy or rhabdomyolysis, such as patients receiving concomitant medications known to cause these conditions and patients with a history of rhabdomyolysis, myopathy or increased serum creatine kinase (6.2).

To report SUSPECTED ADVERSE REACTIONS, contact Merck Sharp & Dohme Corp., a subsidiary of Merck & Co., Inc., at 1-877-888-4231 or FDA at 1-800-FDA-1088 or www.fda.gov/medwatch.

7 DRUG INTERACTIONS

- Coadministration of ISENTRESS and other drugs may alter the plasma concentration of raltegravir. The potential for drug-drug interactions must be considered prior to and during therapy (7).
- Coadministration of ISENTRESS with drugs that are strong inducers of UGT1A1, such as rifampin, may result in reduced plasma concentrations of raltegravir (2.1, 7.2).

8 USE IN SPECIFIC POPULATIONS

Pregnancy:

- ISENTRESS should be used during pregnancy only if the potential benefit justifies the potential risk to the fetus (8.1).

Nursing Mothers:

- Breastfeeding is not recommended while taking ISENTRESS (8.3).

FULL PRESCRIBING INFORMATION

1 INDICATIONS AND USAGE

ISENTRESS® is indicated in combination with other antiretroviral agents for the treatment of human immunodeficiency virus (HIV-1) infection in patients 4 weeks of age and older.

- The use of other active agents with ISENTRESS is associated with a greater likelihood of treatment response [see Clinical Studies (14)] .

2 DOSAGE AND ADMINISTRATION

2.1 General Dosing Recommendations

- ISENTRESS Film-Coated Tablets, Chewable Tablets and For Oral Suspension can be administered with or without food [see Clinical Pharmacology (12.3)] .
- Because the formulations are not bioequivalent, do not substitute ISENTRESS chewable tablets or ISENTRESS for oral suspension for the ISENTRESS 400 mg film-coated tablet. See specific dosing guidance for chewable tablets and the formulation for oral suspension.
- During coadministration of ISENTRESS 400 mg film-coated tablets with rifampin, the recommended dosage of ISENTRESS is 800 mg twice daily in adults. There are no data to guide co-administration of ISENTRESS with rifampin in patients below 18 years of age [see Drug Interactions (7.2)] .
- Maximum dose of chewable tablets is 300 mg twice daily.
- Maximum dose of oral suspension is 100 mg twice daily.
- Each single-use packet for oral suspension contains 100 mg of raltegravir which is suspended in 5 mL of water giving a final concentration of 20 mg/mL.

2.2 Adults

For the treatment of adult patients with HIV-1 infection, the dosage of ISENTRESS is one 400 mg film-coated tablet administered orally, twice daily.

2.3 Pediatrics

- If at least 25 kg: One 400 mg film-coated tablet orally, twice daily.
- If unable to swallow a tablet, consider the chewable tablet, as specified in Table 1.

Table 1: Alternative Dose [The weight-based dosing recommendation for the chewable tablet is based on approximately 6 mg/kg/dose twice daily [see Clinical Pharmacology (12.3)] .] with ISENTRESS Chewable Tablets for Pediatric Patients Weighing at Least 25 kg
Body Weight (kg) | Dose | Number of Chewable Tablets
25 to less than 28 | 150 mg twice daily | 1.5 × 100 mg [The 100 mg chewable tablet can be divided into equal halves.] twice daily
28 to less than 40 | 200 mg twice daily | 2 × 100 mg twice daily
At least 40 | 300 mg twice daily | 3 × 100 mg twice daily

- If at least 4 weeks of age and weighing at least 3 kg to less than 25 kg: Weight based dosing, as specified in Table 2.
- For patients weighing between 11 and 20 kg, either the chewable tablet or oral suspension can be used, as specified in Table 2. Patients can remain on the oral suspension as long as their weight is below 20 kg. Refer to Table 2 for appropriate dosing [see Clinical Studies (14.3)] .

Table 2: Recommended Dose [The weight-based dosing recommendation for the chewable tablet and oral suspension is based on approximately 6 mg/kg/dose twice daily [see Clinical Pharmacology (12.3)] .] for ISENTRESS For Oral Suspension and Chewable Tablets in Pediatric Patients Weighing Less than 25 kg
Body Weight (kg) | Volume (Dose) of Suspension to be Administered | Number of Chewable Tablets
3 to less than 4 | 1 mL (20 mg) twice daily
4 to less than 6 | 1.5 mL (30 mg) twice daily
6 to less than 8 | 2 mL (40 mg) twice daily
8 to less than 11 | 3 mL (60 mg) twice daily
11 to less than 14 [For weight between 11 and 20 kg either formulation can be used. Note: The chewable tablets are available as 25 mg and 100 mg tablets.] | 4 mL (80 mg) twice daily | 3 × 25 mg twice daily
14 to less than 20 | 5 mL (100 mg) twice daily | 1 × 100 mg twice daily
20 to less than 25 |  | 1.5 × 100 mg [The 100 mg chewable tablet can be divided into equal halves.] twice daily

2.4 Method of Administration

ISENTRESS Film-Coated Tablets

- Film-Coated Tablets must be swallowed whole

ISENTRESS Chewable Tablets

- Chewable Tablets may be chewed or swallowed whole

ISENTRESS For Oral Suspension

Each single-use ISENTRESS packet for oral suspension contains 100 mg of raltegravir which is to be suspended in 5 mL of water giving a final concentration of 20 mg/mL.

- Pour packet contents of ISENTRESS for oral suspension into 5 mL of water and mix
- Once mixed, measure the recommended volume (dose) of suspension with a syringe and administer the dose orally
- The volume (dose) of suspension should be administered orally within 30 minutes of mixing
- Discard any remaining suspension
- For more details on preparation and administration of the suspension, see Instructions for Use.

3 DOSAGE FORMS AND STRENGTHS

- Film-coated Tablets
  400 mg pink, oval-shaped, film-coated tablets with "227" on one side.

- Chewable Tablets
  100 mg pale orange, oval-shaped, orange-banana flavored, chewable tablets scored on both sides and imprinted on one face with the Merck logo and "477" on opposite sides of the score.
  25 mg pale yellow, round, orange-banana flavored, chewable tablets with the Merck logo on one side and "473" on the other side.

- For Oral Suspension
  100 mg white to off-white, banana flavored, granular powder that may contain yellow or beige to tan particles in a child resistant single-use foil packet.

4 CONTRAINDICATIONS

None

5 WARNINGS AND PRECAUTIONS

5.1 Severe Skin and Hypersensitivity Reactions

Severe, potentially life-threatening, and fatal skin reactions have been reported. These include cases of Stevens-Johnson syndrome and toxic epidermal necrolysis. Hypersensitivity reactions have also been reported and were characterized by rash, constitutional findings, and sometimes, organ dysfunction, including hepatic failure. Discontinue ISENTRESS and other suspect agents immediately if signs or symptoms of severe skin reactions or hypersensitivity reactions develop (including, but not limited to, severe rash or rash accompanied by fever, general malaise, fatigue, muscle or joint aches, blisters, oral lesions, conjunctivitis, facial edema, hepatitis, eosinophilia, angioedema). Clinical status including liver aminotransferases should be monitored and appropriate therapy initiated. Delay in stopping ISENTRESS treatment or other suspect agents after the onset of severe rash may result in a life-threatening reaction.

5.2 Immune Reconstitution Syndrome

Immune reconstitution syndrome has been reported in patients treated with combination antiretroviral therapy, including ISENTRESS. During the initial phase of combination antiretroviral treatment, patients whose immune systems respond may develop an inflammatory response to indolent or residual opportunistic infections (such as Mycobacterium avium infection, cytomegalovirus, Pneumocystis jiroveci pneumonia, tuberculosis), which may necessitate further evaluation and treatment.

Autoimmune disorders (such as Graves' disease, polymyositis, and Guillain-Barré syndrome) have also been reported to occur in the setting of immune reconstitution; however, the time to onset is more variable, and can occur many months after initiation of treatment.

5.3 Phenylketonurics

ISENTRESS Chewable Tablets contain phenylalanine, a component of aspartame. Each 25 mg ISENTRESS Chewable Tablet contains approximately 0.05 mg phenylalanine. Each 100 mg ISENTRESS Chewable Tablet contains approximately 0.10 mg phenylalanine. Phenylalanine can be harmful to patients with phenylketonuria.

6 ADVERSE REACTIONS

Because clinical trials are conducted under widely varying conditions, adverse reaction rates observed in the clinical trials of a drug cannot be directly compared to rates in the clinical trials of another drug and may not reflect the rates observed in practice.

6.1 Clinical Trials Experience

Treatment-Naïve Adults

The following safety assessment of ISENTRESS in treatment-naïve subjects is based on the randomized double-blind active controlled study of treatment-naïve subjects, STARTMRK (Protocol 021) with ISENTRESS 400 mg twice daily in combination with a fixed dose of emtricitabine 200 mg (+) tenofovir 300 mg, (N=281) versus efavirenz (EFV) 600 mg at bedtime in combination with emtricitabine (+) tenofovir, (N=282). During double-blind treatment, the total follow-up for subjects receiving ISENTRESS 400 mg twice daily + emtricitabine (+) tenofovir was 1104 patient-years and 1036 patient-years for subjects receiving efavirenz 600 mg at bedtime + emtricitabine (+) tenofovir.

In Protocol 021, the rate of discontinuation of therapy due to adverse events was 5% in subjects receiving ISENTRESS + emtricitabine (+) tenofovir and 10% in subjects receiving efavirenz + emtricitabine (+) tenofovir.

The clinical adverse drug reactions (ADRs) listed below were considered by investigators to be causally related to ISENTRESS + emtricitabine (+) tenofovir or efavirenz + emtricitabine (+) tenofovir. Clinical ADRs of moderate to severe intensity occurring in ≥2% of treatment-naïve subjects treated with ISENTRESS are presented in Table 3.

Table 3: Adverse Drug Reactions [Includes adverse experiences considered by investigators to be at least possibly, probably, or definitely related to the drug.] of Moderate to Severe Intensity [Intensities are defined as follows: Moderate (discomfort enough to cause interference with usual activity); Severe (incapacitating with inability to work or do usual activity).] Occurring in ≥2% of Treatment-Naïve Adult Subjects Receiving ISENTRESS (240 Week Analysis)
System Organ Class, Preferred Term | Randomized Study Protocol 021
System Organ Class, Preferred Term | ISENTRESS 400 mg Twice Daily + Emtricitabine (+) Tenofovir (n = 281) | Efavirenz 600 mg At Bedtime + Emtricitabine (+) Tenofovir (n = 282)
Gastrointestinal Disorders
Nausea | 3% | 4%
General Disorders and Administration
Fatigue | 2% | 3%
Nervous System Disorders
Headache | 4% | 5%
Dizziness | 2% | 6%
Psychiatric Disorders
Insomnia | 4% | 4%
n = total number of subjects per treatment group

Laboratory Abnormalities

The percentages of adult subjects treated with ISENTRESS 400 mg twice daily or efavirenz in Protocol 021 with selected Grades 2 to 4 laboratory abnormalities that represent a worsening Grade from baseline are presented in Table 4.

Table 4: Selected Grade 2 to 4 Laboratory Abnormalities Reported in Treatment-Naïve Subjects (240 Week Analysis)
 |  | Randomized Study Protocol 021
Laboratory Parameter Preferred Term (Unit) | Limit | ISENTRESS 400 mg Twice Daily + Emtricitabine (+) Tenofovir (N = 281) | Efavirenz 600 mg At Bedtime + Emtricitabine (+) Tenofovir (N = 282)
Hematology
Absolute neutrophil count (10^3/µL)
Grade 2 | 0.75 - 0.999 | 3% | 5%
Grade 3 | 0.50 - 0.749 | 3% | 1%
Grade 4 | <0.50 | 1% | 1%
Hemoglobin (gm/dL)
Grade 2 | 7.5 - 8.4 | 1% | 1%
Grade 3 | 6.5 - 7.4 | 1% | 1%
Grade 4 | <6.5 | <1% | 0%
Platelet count (10^3/µL)
Grade 2 | 50 - 99.999 | 1% | 0%
Grade 3 | 25 - 49.999 | <1% | <1%
Grade 4 | <25 | 0% | 0%
Blood chemistry
Fasting (non-random) serum glucose test (mg/dL)
Grade 2 | 126 - 250 | 7% | 6%
Grade 3 | 251 - 500 | 2% | 1%
Grade 4 | >500 | 0% | 0%
Total serum bilirubin
Grade 2 | 1.6 - 2.5 × ULN | 5% | <1%
Grade 3 | 2.6 - 5.0 × ULN | 1% | 0%
Grade 4 | >5.0 × ULN | <1% | 0%
Serum aspartate aminotransferase
Grade 2 | 2.6 - 5.0 × ULN | 8% | 10%
Grade 3 | 5.1 - 10.0 × ULN | 5% | 3%
Grade 4 | >10.0 × ULN | 1% | <1%
Serum alanine aminotransferase
Grade 2 | 2.6 - 5.0 × ULN | 11% | 12%
Grade 3 | 5.1 - 10.0 × ULN | 2% | 2%
Grade 4 | >10.0 × ULN | 2% | 1%
Serum alkaline phosphatase
Grade 2 | 2.6 - 5.0 × ULN | 1% | 3%
Grade 3 | 5.1 - 10.0 × ULN | 0% | 1%
Grade 4 | >10.0 × ULN | <1% | <1%
ULN = Upper limit of normal range

Lipids, Change from Baseline

Changes from baseline in fasting lipids are shown in Table 5.

Table 5: Lipid Values, Mean Change from Baseline, Protocol 021
Laboratory Parameter Preferred Term | ISENTRESS 400 mg Twice Daily + Emtricitabine (+) Tenofovir N = 207 |  |  | Efavirenz 600 mg At Bedtime + Emtricitabine (+) Tenofovir N = 187
 |  |  | Change from Baseline at Week 240 |  |  | Change from Baseline at Week 240
 | Baseline Mean | Week 240 Mean | Mean Change | Baseline Mean | Week 240 Mean | Mean Change
 | (mg/dL) | (mg/dL) | (mg/dL) | (mg/dL) | (mg/dL) | (mg/dL)
LDL-Cholesterol [Fasting (non-random) laboratory tests at Week 240.] | 96 | 106 | 10 | 93 | 118 | 25
HDL-Cholesterol | 38 | 44 | 6 | 38 | 51 | 13
Total Cholesterol | 159 | 175 | 16 | 157 | 201 | 44
Triglyceride | 128 | 130 | 2 | 141 | 178 | 37
Notes:
N = total number of subjects per treatment group with at least one lipid test result available. The analysis is based on all available data.
If subjects initiated or increased serum lipid-reducing agents, the last available lipid values prior to the change in therapy were used in the analysis. If the missing data was due to other reasons, subjects were censored thereafter for the analysis. At baseline, serum lipid-reducing agents were used in 5% of subjects in the group receiving ISENTRESS and 3% in the efavirenz group. Through Week 240, serum lipid-reducing agents were used in 9% of subjects in the group receiving ISENTRESS and 15% in the efavirenz group.

Treatment-Experienced Adults

The safety assessment of ISENTRESS in treatment-experienced subjects is based on the pooled safety data from the randomized, double-blind, placebo-controlled trials, BENCHMRK 1 and BENCHMRK 2 (Protocols 018 and 019) in antiretroviral treatment-experienced HIV-1 infected adult subjects. A total of 462 subjects received the recommended dose of ISENTRESS 400 mg twice daily in combination with optimized background therapy (OBT) compared to 237 subjects taking placebo in combination with OBT. The median duration of therapy in these trials was 96 weeks for subjects receiving ISENTRESS and 38 weeks for subjects receiving placebo. The total exposure to ISENTRESS was 708 patient-years versus 244 patient-years on placebo. The rates of discontinuation due to adverse events were 4% in subjects receiving ISENTRESS and 5% in subjects receiving placebo.

Clinical ADRs were considered by investigators to be causally related to ISENTRESS + OBT or placebo + OBT. Clinical ADRs of moderate to severe intensity occurring in ≥2% of subjects treated with ISENTRESS and occurring at a higher rate compared to placebo are presented in Table 6.

Table 6: Adverse Drug Reactions [Includes adverse reactions at least possibly, probably, or definitely related to the drug.] of Moderate to Severe Intensity [Intensities are defined as follows: Moderate (discomfort enough to cause interference with usual activity); Severe (incapacitating with inability to work or do usual activity).] Occurring in ≥2% of Treatment-Experienced Adult Subjects Receiving ISENTRESS and at a Higher Rate Compared to Placebo (96 Week Analysis)
System Organ Class, Adverse Reactions | Randomized Studies Protocol 018 and 019
System Organ Class, Adverse Reactions | ISENTRESS 400 mg Twice Daily + OBT (n = 462) | Placebo + OBT (n = 237)
Nervous System Disorders
Headache | 2% | <1%
n=total number of subjects per treatment group.

Laboratory Abnormalities

The percentages of adult subjects treated with ISENTRESS 400 mg twice daily or placebo in Protocols 018 and 019 with selected Grade 2 to 4 laboratory abnormalities representing a worsening Grade from baseline are presented in Table 7.

Table 7: Selected Grade 2 to 4 Laboratory Abnormalities Reported in Treatment-Experienced Subjects (96 Week Analysis)
 |  | Randomized Studies Protocol 018 and 019
Laboratory Parameter Preferred Term (Unit) | Limit | ISENTRESS 400 mg Twice Daily + OBT (N = 462) | Placebo + OBT (N = 237)
Hematology
Absolute neutrophil count (10^3/µL)
Grade 2 | 0.75 - 0.999 | 4% | 5%
Grade 3 | 0.50 - 0.749 | 3% | 3%
Grade 4 | <0.50 | 1% | <1%
Hemoglobin (gm/dL)
Grade 2 | 7.5 - 8.4 | 1% | 3%
Grade 3 | 6.5 - 7.4 | 1% | 1%
Grade 4 | <6.5 | <1% | 0%
Platelet count (10^3/µL)
Grade 2 | 50 - 99.999 | 3% | 5%
Grade 3 | 25 - 49.999 | 1% | <1%
Grade 4 | <25 | 1% | <1%
Blood chemistry
Fasting (non-random) serum glucose test (mg/dL)
Grade 2 | 126 - 250 | 10% | 7%
Grade 3 | 251 - 500 | 3% | 1%
Grade 4 | >500 | 0% | 0%
Total serum bilirubin
Grade 2 | 1.6 - 2.5 × ULN | 6% | 3%
Grade 3 | 2.6 - 5.0 × ULN | 3% | 3%
Grade 4 | >5.0 × ULN | 1% | 0%
Serum aspartate aminotransferase
Grade 2 | 2.6 - 5.0 × ULN | 9% | 7%
Grade 3 | 5.1 - 10.0 × ULN | 4% | 3%
Grade 4 | >10.0 × ULN | 1% | 1%
Serum alanine aminotransferase
Grade 2 | 2.6 - 5.0 × ULN | 9% | 9%
Grade 3 | 5.1 - 10.0 × ULN | 4% | 2%
Grade 4 | >10.0 × ULN | 1% | 2%
Serum alkaline phosphatase
Grade 2 | 2.6 - 5.0 × ULN | 2% | <1%
Grade 3 | 5.1 - 10.0 × ULN | <1% | 1%
Grade 4 | >10.0 × ULN | 1% | <1%
Serum pancreatic amylase test
Grade 2 | 1.6 - 2.0 × ULN | 2% | 1%
Grade 3 | 2.1 - 5.0 × ULN | 4% | 3%
Grade 4 | >5.0 × ULN | <1% | <1%
Serum lipase test
Grade 2 | 1.6 - 3.0 × ULN | 5% | 4%
Grade 3 | 3.1 - 5.0 × ULN | 2% | 1%
Grade 4 | >5.0 × ULN | 0% | 0%
Serum creatine kinase
Grade 2 | 6.0 - 9.9 × ULN | 2% | 2%
Grade 3 | 10.0 - 19.9 × ULN | 4% | 3%
Grade 4 | ≥20.0 × ULN | 3% | 1%
ULN = Upper limit of normal range

Less Common Adverse Reactions Observed in Treatment-Naïve and Treatment-Experienced Studies

The following ADRs occurred in <2% of treatment-naïve or treatment-experienced subjects receiving ISENTRESS in a combination regimen. These events have been included because of their seriousness, increased frequency on ISENTRESS compared with efavirenz or placebo, or investigator's assessment of potential causal relationship.

Gastrointestinal Disorders: abdominal pain, gastritis, dyspepsia, vomiting

General Disorders and Administration Site Conditions: asthenia

Hepatobiliary Disorders: hepatitis

Immune System Disorders: hypersensitivity

Infections and Infestations: genital herpes, herpes zoster

Psychiatric Disorders: depression (particularly in subjects with a pre-existing history of psychiatric illness), including suicidal ideation and behaviors

Renal and Urinary Disorders: nephrolithiasis, renal failure

Selected Adverse Events - Adults

Cancers were reported in treatment-experienced subjects who initiated ISENTRESS or placebo, both with OBT, and in treatment-naïve subjects who initiated ISENTRESS or efavirenz, both with emtricitabine (+) tenofovir; several were recurrent. The types and rates of specific cancers were those expected in a highly immunodeficient population (many had CD4+ counts below 50 cells/mm^3 and most had prior AIDS diagnoses). The risk of developing cancer in these studies was similar in the group receiving ISENTRESS and the group receiving the comparator.

Grade 2-4 creatine kinase laboratory abnormalities were observed in subjects treated with ISENTRESS (see Table 7). Myopathy and rhabdomyolysis have been reported. Use with caution in patients at increased risk of myopathy or rhabdomyolysis, such as patients receiving concomitant medications known to cause these conditions and patients with a history of rhabdomyolysis, myopathy or increased serum creatine kinase.

Rash occurred more commonly in treatment-experienced subjects receiving regimens containing ISENTRESS + darunavir/ritonavir compared to subjects receiving ISENTRESS without darunavir/ritonavir or darunavir/ritonavir without ISENTRESS. However, rash that was considered drug related occurred at similar rates for all three groups. These rashes were mild to moderate in severity and did not limit therapy; there were no discontinuations due to rash.

Patients with Co-existing Conditions - Adults

Patients Co-infected with Hepatitis B and/or Hepatitis C Virus

In the randomized, double-blind, placebo-controlled trials, treatment-experienced subjects (N = 114/699 or 16%) and treatment-naïve subjects (N = 34/563 or 6%) with chronic (but not acute) active hepatitis B and/or hepatitis C virus co-infection were permitted to enroll provided that baseline liver function tests did not exceed 5 times the upper limit of normal (ULN). In general the safety profile of ISENTRESS in subjects with hepatitis B and/or hepatitis C virus co-infection was similar to that in subjects without hepatitis B and/or hepatitis C virus co-infection, although the rates of AST and ALT abnormalities were higher in the subgroup with hepatitis B and/or hepatitis C virus co-infection for all treatment groups. At 96 weeks, in treatment-experienced subjects, Grade 2 or higher laboratory abnormalities that represent a worsening Grade from baseline of AST, ALT or total bilirubin occurred in 29%, 34% and 13%, respectively, of co-infected subjects treated with ISENTRESS as compared to 11%, 10% and 9% of all other subjects treated with ISENTRESS. At 240 weeks, in treatment-naïve subjects, Grade 2 or higher laboratory abnormalities that represent a worsening Grade from baseline of AST, ALT or total bilirubin occurred in 22%, 44% and 17%, respectively, of co-infected subjects treated with ISENTRESS as compared to 13%, 13% and 5% of all other subjects treated with ISENTRESS.

Pediatrics

2 to 18 Years of Age

ISENTRESS has been studied in 126 antiretroviral treatment-experienced HIV-1 infected children and adolescents 2 to 18 years of age, in combination with other antiretroviral agents in IMPAACT P1066 [see Use in Specific Populations (8.4) and Clinical Studies (14.3)] . Of the 126 patients, 96 received the recommended dose of ISENTRESS.

In these 96 children and adolescents, frequency, type and severity of drug related adverse reactions through Week 24 were comparable to those observed in adults.

One patient experienced drug related clinical adverse reactions of Grade 3 psychomotor hyperactivity, abnormal behavior and insomnia; one patient experienced a Grade 2 serious drug related allergic rash.

One patient experienced drug related laboratory abnormalities, Grade 4 AST and Grade 3 ALT, which were considered serious.

4 Weeks to less than 2 Years of Age

ISENTRESS has also been studied in 26 HIV-1 infected infants and toddlers 4 weeks to less than 2 years of age, in combination with other antiretroviral agents in IMPAACT P1066 [see Use in Specific Populations (8.4) and Clinical Studies (14.3)] .

In these 26 infants and toddlers, the frequency, type and severity of drug-related adverse reactions through Week 48 were comparable to those observed in adults.

One patient experienced a Grade 3 serious drug-related allergic rash that resulted in treatment discontinuation.

6.2 Postmarketing Experience

The following adverse reactions have been identified during postapproval use of ISENTRESS. Because these reactions are reported voluntarily from a population of uncertain size, it is not always possible to reliably estimate their frequency or establish a causal relationship to drug exposure.

Blood and Lymphatic System Disorders: thrombocytopenia

Gastrointestinal Disorders: diarrhea

Hepatobiliary Disorders: hepatic failure (with and without associated hypersensitivity) in patients with underlying liver disease and/or concomitant medications

Musculoskeletal and Connective Tissue Disorders: rhabdomyolysis

Nervous System Disorders: cerebellar ataxia

Psychiatric Disorders: anxiety, paranoia

7 DRUG INTERACTIONS

7.1 Effect of Raltegravir on the Pharmacokinetics of Other Agents

Raltegravir does not inhibit (IC50>100 µM) CYP1A2, CYP2B6, CYP2C8, CYP2C9, CYP2C19, CYP2D6 or CYP3A in vitro. Moreover, in vitro, raltegravir did not induce CYP1A2, CYP2B6 or CYP3A4. A midazolam drug interaction study confirmed the low propensity of raltegravir to alter the pharmacokinetics of agents metabolized by CYP3A4 in vivo by demonstrating a lack of effect of raltegravir on the pharmacokinetics of midazolam, a sensitive CYP3A4 substrate. Similarly, raltegravir is not an inhibitor (IC50>50 µM) of UGT1A1 or UGT2B7, and raltegravir does not inhibit P-glycoprotein-mediated transport. Based on these data, ISENTRESS is not expected to affect the pharmacokinetics of drugs that are substrates of these enzymes or P-glycoprotein (e.g., protease inhibitors, NNRTIs, opioid analgesics, statins, azole antifungals, proton pump inhibitors and anti-erectile dysfunction agents).

7.2 Effect of Other Agents on the Pharmacokinetics of Raltegravir

Raltegravir is not a substrate of cytochrome P450 (CYP) enzymes. Based on in vivo and in vitro studies, raltegravir is eliminated mainly by metabolism via a UGT1A1-mediated glucuronidation pathway. Coadministration of ISENTRESS with drugs that inhibit UGT1A1 may increase plasma levels of raltegravir and coadministration of ISENTRESS with drugs that induce UGT1A1, such as rifampin, may reduce plasma levels of raltegravir.

The impact of other inducers of drug metabolizing enzymes, such as phenytoin and phenobarbital, on UGT1A1 is unknown.

Selected drug interactions are presented in Table 8 [see Clinical Pharmacology (12.3)] .

Table 8: Selected Drug Interactions in Adults
Concomitant Drug Class: Drug Name | Effect on Concentration of Raltegravir | Clinical Comment
Metal-Containing Antacids
aluminum and/or magnesium-containing antacids | ↓ | Coadministration or staggered administration of aluminum and/or magnesium hydroxide-containing antacids and ISENTRESS is not recommended.
Other Agents
rifampin | ↓ | The recommended dosage of ISENTRESS is 800 mg twice daily during coadministration with rifampin. There are no data to guide co-administration of ISENTRESS with rifampin in patients below 18 years of age [see Dosage and Administration (2.1)].

7.3 Drugs without Clinically Significant Interactions with ISENTRESS

In drug interaction studies, raltegravir did not have a clinically meaningful effect on the pharmacokinetics of the following: hormonal contraceptives, methadone, lamivudine, tenofovir, etravirine, darunavir/ritonavir, or boceprevir. Moreover, atazanavir, atazanavir/ritonavir, boceprevir, calcium carbonate antacids, darunavir/ritonavir, efavirenz, etravirine, omeprazole, or tipranavir/ritonavir did not have a clinically meaningful effect on the pharmacokinetics of raltegravir. No dose adjustment is required when ISENTRESS is coadministered with these drugs.

8 USE IN SPECIFIC POPULATIONS

8.1 Pregnancy

TERATOGENIC EFFECTS

Pregnancy Category C

ISENTRESS should be used during pregnancy only if the potential benefit justifies the potential risk to the fetus. There are no adequate and well-controlled studies in pregnant women. In addition, there have been no pharmacokinetic studies conducted in pregnant patients.

Developmental toxicity studies were performed in rabbits (at oral doses up to 1000 mg/kg/day) and rats (at oral doses up to 600 mg/kg/day). The reproductive toxicity study in rats was performed with pre-, peri-, and postnatal evaluation. The highest doses in these studies produced systemic exposures in these species approximately 3- to 4-fold the exposure at the recommended human dose. In both rabbits and rats, no treatment-related effects on embryonic/fetal survival or fetal weights were observed. In addition, no treatment-related external, visceral, or skeletal changes were observed in rabbits. However, treatment-related increases over controls in the incidence of supernumerary ribs were seen in rats at 600 mg/kg/day (exposures 3-fold the exposure at the recommended human dose).

Placenta transfer of drug was demonstrated in both rats and rabbits. At a maternal dose of 600 mg/kg/day in rats, mean drug concentrations in fetal plasma were approximately 1.5- to 2.5-fold greater than in maternal plasma at 1 hour and 24 hours postdose, respectively. Mean drug concentrations in fetal plasma were approximately 2% of the mean maternal concentration at both 1 and 24 hours postdose at a maternal dose of 1000 mg/kg/day in rabbits.

Antiretroviral Pregnancy Registry

To monitor maternal-fetal outcomes of pregnant patients exposed to ISENTRESS, an Antiretroviral Pregnancy Registry has been established. Physicians are encouraged to register patients by calling 1-800-258-4263.

8.3 Nursing Mothers

Breastfeeding is not recommended while taking ISENTRESS. In addition, it is recommended that HIV-1-infected mothers not breastfeed their infants to avoid risking postnatal transmission of HIV-1.

It is not known whether raltegravir is secreted in human milk. However, raltegravir is secreted in the milk of lactating rats. Mean drug concentrations in milk were approximately 3-fold greater than those in maternal plasma at a maternal dose of 600 mg/kg/day in rats. There were no effects in rat offspring attributable to exposure of ISENTRESS through the milk.

8.4 Pediatric Use

The safety, tolerability, pharmacokinetic profile, and efficacy of ISENTRESS were evaluated in HIV-1 infected infants, children and adolescents 4 weeks to 18 years of age in an open-label, multicenter clinical trial, IMPAACT P1066 [see Clinical Pharmacology (12.3) and Clinical Studies (14.3)] . The safety profile was comparable to that observed in adults [see Adverse Reactions (6.1)] . See Dosage and Administration (2.3) for dosing recommendations for children 4 weeks of age and older. The safety and dosing information for ISENTRESS have not been established in infants less than 4 weeks of age.

8.5 Geriatric Use

Clinical studies of ISENTRESS did not include sufficient numbers of subjects aged 65 and over to determine whether they respond differently from younger subjects. Other reported clinical experience has not identified differences in responses between the elderly and younger subjects. In general, dose selection for an elderly patient should be cautious, reflecting the greater frequency of decreased hepatic, renal, or cardiac function, and of concomitant disease or other drug therapy.

8.6 Use in Patients with Hepatic Impairment

No clinically important pharmacokinetic differences between subjects with moderate hepatic impairment and healthy subjects were observed. No dosage adjustment is necessary for patients with mild to moderate hepatic impairment. The effect of severe hepatic impairment on the pharmacokinetics of raltegravir has not been studied [see Clinical Pharmacology (12.3)].

8.7 Use in Patients with Renal Impairment

No clinically important pharmacokinetic differences between subjects with severe renal impairment and healthy subjects were observed. No dosage adjustment is necessary [see Clinical Pharmacology (12.3)].

10 OVERDOSAGE

No specific information is available on the treatment of overdosage with ISENTRESS. Doses as high as 1600-mg single dose and 800-mg twice-daily multiple doses were studied in healthy volunteers without evidence of toxicity. Occasional doses of up to 1800 mg per day were taken in the clinical studies of HIV-1 infected subjects without evidence of toxicity.

In the event of an overdose, it is reasonable to employ the standard supportive measures, e.g., remove unabsorbed material from the gastrointestinal tract, employ clinical monitoring (including obtaining an electrocardiogram), and institute supportive therapy if required. The extent to which ISENTRESS may be dialyzable is unknown.

11 DESCRIPTION

ISENTRESS contains raltegravir potassium, a human immunodeficiency virus integrase strand transfer inhibitor. The chemical name for raltegravir potassium is N-[(4-Fluorophenyl) methyl]-1,6-dihydro-5-hydroxy-1-methyl-2-[1-methyl-1-[[(5-methyl-1,3,4-oxadiazol-2-yl)carbonyl]amino]ethyl]-6-oxo-4-pyrimidinecarboxamide monopotassium salt.

The empirical formula is C20H20FKN6O5 and the molecular weight is 482.51. The structural formula is:

Raltegravir potassium is a white to off-white powder. It is soluble in water, slightly soluble in methanol, very slightly soluble in ethanol and acetonitrile and insoluble in isopropanol.

Each 400 mg film-coated tablet of ISENTRESS for oral administration contains 434.4 mg of raltegravir (as potassium salt), equivalent to 400 mg of raltegravir free phenol and the following inactive ingredients: calcium phosphate dibasic anhydrous, hypromellose 2208, lactose monohydrate, magnesium stearate, microcrystalline cellulose, poloxamer 407 (contains 0.01% butylated hydroxytoluene as antioxidant), sodium stearyl fumarate. In addition, the film coating contains the following inactive ingredients: black iron oxide, polyethylene glycol 3350, polyvinyl alcohol, red iron oxide, talc and titanium dioxide.

Each 100 mg chewable tablet of ISENTRESS for oral administration contains 108.6 mg of raltegravir (as potassium salt), equivalent to 100 mg of raltegravir free phenol and the following inactive ingredients: ammonium hydroxide, crospovidone, ethylcellulose 20 cP, fructose, hydroxypropyl cellulose, hypromellose 2910/6cP, magnesium stearate, mannitol, medium chain triglycerides, monoammonium glycyrrhizinate, natural and artificial flavors (orange, banana, and masking that contains aspartame), oleic acid, PEG 400, red iron oxide, saccharin sodium, sodium citrate dihydrate, sodium stearyl fumarate, sorbitol, sucralose and yellow iron oxide.

Each 25 mg chewable tablet of ISENTRESS for oral administration contains 27.16 mg of raltegravir (as potassium salt), equivalent to 25 mg of raltegravir free phenol and the following inactive ingredients: ammonium hydroxide, crospovidone, ethylcellulose 20 cP, fructose, hydroxypropyl cellulose, hypromellose 2910/6cP, magnesium stearate, mannitol, medium chain triglycerides, monoammonium glycyrrhizinate, natural and artificial flavors (orange, banana, and masking that contains aspartame), oleic acid, PEG 400, saccharin sodium, sodium citrate dihydrate, sodium stearyl fumarate, sorbitol, sucralose and yellow iron oxide.

Each packet of ISENTRESS for oral suspension 100 mg, contains 108.6 mg of raltegravir (as potassium salt), equivalent to 100 mg of raltegravir free phenol and the following inactive ingredients: ammonium hydroxide, banana with other natural flavors, carboxymethylcellulose sodium, crospovidone, ethylcellulose 20 cP, fructose, hydroxypropyl cellulose, hypromellose 2910/6cP, macrogol/PEG 400, magnesium stearate, maltodextrin, mannitol, medium chain triglycerides, microcrystalline cellulose, monoammonium glycyrrhizinate, oleic acid, sorbitol, sucralose and sucrose.

12 CLINICAL PHARMACOLOGY

12.1 Mechanism of Action

Raltegravir is an HIV-1 antiviral drug [see Microbiology (12.4)] .

12.2 Pharmacodynamics

In a monotherapy study raltegravir (400 mg twice daily) demonstrated rapid antiviral activity with mean viral load reduction of 1.66 log10 copies/mL by Day 10.

In the randomized, double-blind, placebo-controlled, dose-ranging trial, Protocol 005, and Protocols 018 and 019, antiviral responses were similar among subjects regardless of dose.

Effects on Electrocardiogram

In a randomized, placebo-controlled, crossover study, 31 healthy subjects were administered a single oral supratherapeutic dose of raltegravir 1600 mg and placebo. Peak raltegravir plasma concentrations were approximately 4-fold higher than the peak concentrations following a 400 mg dose. ISENTRESS did not appear to prolong the QTc interval for 12 hours postdose. After baseline and placebo adjustment, the maximum mean QTc change was -0.4 msec (1-sided 95% upper Cl: 3.1 msec).

12.3 Pharmacokinetics

Adults

Absorption

Raltegravir (film-coated tablet) is absorbed with a Tmax of approximately 3 hours postdose in the fasted state. Raltegravir AUC and Cmax increase dose proportionally over the dose range 100 mg to 1600 mg. Raltegravir C12hr increases dose proportionally over the dose range of 100 to 800 mg and increases slightly less than dose proportionally over the dose range 100 mg to 1600 mg. With twice-daily dosing, pharmacokinetic steady state is achieved within approximately the first 2 days of dosing. There is little to no accumulation in AUC and Cmax. The average accumulation ratio for C12hr ranged from approximately 1.2 to 1.6.

The absolute bioavailability of raltegravir has not been established. Based on a formulation comparison study in healthy adult volunteers, the chewable tablet and oral suspension have higher oral bioavailability compared to the 400 mg film-coated tablet.

In subjects who received 400 mg twice daily alone, raltegravir drug exposures were characterized by a geometric mean AUC0-12hr of 14.3 µM∙hr and C12hr of 142 nM.

Considerable variability was observed in the pharmacokinetics of raltegravir. For observed C12hr in Protocols 018 and 019, the coefficient of variation (CV) for inter-subject variability = 212% and the CV for intra-subject variability = 122%.

Effect of Food on Oral Absorption

ISENTRESS may be administered with or without food. Raltegravir was administered without regard to food in the pivotal safety and efficacy studies in HIV-1-infected patients. The effect of consumption of low-, moderate- and high-fat meals on steady-state raltegravir pharmacokinetics was assessed in healthy volunteers administered the 400 mg film-coated tablet. Administration of multiple doses of raltegravir following a moderate-fat meal (600 Kcal, 21 g fat) did not affect raltegravir AUC to a clinically meaningful degree with an increase of 13% relative to fasting. Raltegravir C12hr was 66% higher and Cmax was 5% higher following a moderate-fat meal compared to fasting. Administration of raltegravir following a high-fat meal (825 Kcal, 52 g fat) increased AUC and Cmax by approximately 2-fold and increased C12hr by 4.1-fold. Administration of raltegravir following a low-fat meal (300 Kcal, 2.5 g fat) decreased AUC and Cmax by 46% and 52%, respectively; C12hr was essentially unchanged. Food appears to increase pharmacokinetic variability relative to fasting.

Administration of the chewable tablet with a high fat meal led to an average 6% decrease in AUC, 62% decrease in Cmax, and 188% increase in C12hr compared to administration in the fasted state. Administration of the chewable tablet with a high fat meal does not affect raltegravir pharmacokinetics to a clinically meaningful degree and the chewable tablet can be administered without regard to food.

The effect of food on the formulation for oral suspension was not studied.

Distribution

Raltegravir is approximately 83% bound to human plasma protein over the concentration range of 2 to 10 µM.

In one study of HIV-1 infected subjects who received raltegravir 400 mg twice daily, raltegravir was measured in the cerebrospinal fluid. In the study (n=18), the median cerebrospinal fluid concentration was 5.8% (range 1 to 53.5%) of the corresponding plasma concentration. This median proportion was approximately 3-fold lower than the free fraction of raltegravir in plasma. The clinical relevance of this finding is unknown.

Metabolism and Excretion

The apparent terminal half-life of raltegravir is approximately 9 hours, with a shorter α-phase half-life (~1 hour) accounting for much of the AUC. Following administration of an oral dose of radiolabeled raltegravir, approximately 51 and 32% of the dose was excreted in feces and urine, respectively. In feces, only raltegravir was present, most of which is likely derived from hydrolysis of raltegravir-glucuronide secreted in bile as observed in preclinical species. Two components, namely raltegravir and raltegravir-glucuronide, were detected in urine and accounted for approximately 9 and 23% of the dose, respectively. The major circulating entity was raltegravir and represented approximately 70% of the total radioactivity; the remaining radioactivity in plasma was accounted for by raltegravir-glucuronide. Studies using isoform-selective chemical inhibitors and cDNA-expressed UDP-glucuronosyltransferases (UGT) show that UGT1A1 is the main enzyme responsible for the formation of raltegravir-glucuronide. Thus, the data indicate that the major mechanism of clearance of raltegravir in humans is UGT1A1-mediated glucuronidation.

Special Populations

Pediatric

Two pediatric formulations were evaluated in healthy adult volunteers, where the chewable tablet and oral suspension were compared to the 400 mg tablet. The chewable tablet and oral suspension demonstrated higher oral bioavailability, thus higher AUC, compared to the 400 mg tablet. In the same study, the oral suspension resulted in higher oral bioavailability compared to the chewable tablet. These observations resulted in proposed pediatric doses targeting 6 mg/kg/dose for the chewable tablets and oral suspension. As displayed in Table 9, the doses recommended for HIV-infected infants, children and adolescents 4 weeks to 18 years of age [see Dosage and Administration (2.3)] resulted in a pharmacokinetic profile of raltegravir similar to that observed in adults receiving 400 mg twice daily.

Overall, dosing in pediatric patients achieved exposures (Ctrough) above 45 nM in the majority of subjects, but some differences in exposures between formulations were observed. Pediatric patients above 25 kg administered the chewable tablets had lower trough concentrations (113 nM) compared to pediatric patients above 25 kg administered the 400 mg tablet formulation (233 nM) [see Clinical Studies (14.3)] . As a result, the 400 mg film-coated tablet is the recommended dose in patients weighing at least 25 kg; however, the chewable tablet offers an alternative regimen in patients weighing at least 25 kg who are unable to swallow the film-coated tablet [see Dosage and Administration (2.3)] . In addition, pediatric patients weighing 11 to 25 kg who were administered the chewable tablets had the lowest trough concentrations (82 nM) compared to all other pediatric subgroups.

Table 9: Raltegravir Steady State Pharmacokinetic Parameters in Pediatric Patients Following Administration of Recommended Doses
Body Weight | Formulation | Dose | N [Number of patients with intensive pharmacokinetic (PK) results at the final recommended dose.] | Geometric Mean (%CV [Geometric coefficient of variation.]) AUC0-12hr (µM∙hr) | Geometric Mean (%CV) C12hr (nM)
≥25 kg | Film-coated tablet | 400 mg twice daily | 18 | 14.1 (121%) | 233 (157%)
≥25 kg | Chewable tablet | Weight based dosing, see Table 1 | 9 | 22.1 (36%) | 113 (80%)
11 to less than 25 kg | Chewable tablet | Weight based dosing, see Table 2 | 13 | 18.6 (68%) | 82 (123%)
3 to less than 20 kg | Oral suspension | Weight based dosing, see Table 2 | 19 | 24.5 (43%) | 113 (69%)

The pharmacokinetics of raltegravir in infants under 4 weeks of age has not been established.

Age

The effect of age (18 years and older) on the pharmacokinetics of raltegravir was evaluated in the composite analysis. No dosage adjustment is necessary.

Race

The effect of race on the pharmacokinetics of raltegravir in adults was evaluated in the composite analysis. No dosage adjustment is necessary.

Gender

A study of the pharmacokinetics of raltegravir was performed in healthy adult males and females. Additionally, the effect of gender was evaluated in a composite analysis of pharmacokinetic data from 103 healthy subjects and 28 HIV-1 infected subjects receiving raltegravir monotherapy with fasted administration. No dosage adjustment is necessary.

Hepatic Impairment

Raltegravir is eliminated primarily by glucuronidation in the liver. A study of the pharmacokinetics of raltegravir was performed in adult subjects with moderate hepatic impairment. Additionally, hepatic impairment was evaluated in the composite pharmacokinetic analysis. There were no clinically important pharmacokinetic differences between subjects with moderate hepatic impairment and healthy subjects. No dosage adjustment is necessary for patients with mild to moderate hepatic impairment. The effect of severe hepatic impairment on the pharmacokinetics of raltegravir has not been studied.

Renal Impairment

Renal clearance of unchanged drug is a minor pathway of elimination. A study of the pharmacokinetics of raltegravir was performed in adult subjects with severe renal impairment. Additionally, renal impairment was evaluated in the composite pharmacokinetic analysis. There were no clinically important pharmacokinetic differences between subjects with severe renal impairment and healthy subjects. No dosage adjustment is necessary. Because the extent to which ISENTRESS may be dialyzable is unknown, dosing before a dialysis session should be avoided.

UGT1A1 Polymorphism

There is no evidence that common UGT1A1 polymorphisms alter raltegravir pharmacokinetics to a clinically meaningful extent. In a comparison of 30 adult subjects with *28/*28 genotype (associated with reduced activity of UGT1A1) to 27 adult subjects with wild-type genotype, the geometric mean ratio (90% CI) of AUC was 1.41 (0.96, 2.09).

Drug Interactions [see Drug Interactions (7)]

Table 10: Effect of Other Agents on the Pharmacokinetics of Raltegravir in Adults
Coadministered Drug | Coadministered Drug Dose/Schedule | Raltegravir Dose/Schedule | Ratio (90% Confidence Interval) of Raltegravir Pharmacokinetic Parameters with/without Coadministered Drug; No Effect = 1.00
Coadministered Drug | Coadministered Drug Dose/Schedule | Raltegravir Dose/Schedule | n | Cmax | AUC | Cmin
aluminum and magnesium hydroxide antacid | 20 mL single dose given with raltegravir | 400 mg twice daily | 25 | 0.56 (0.42, 0.73) | 0.51 (0.40, 0.65) | 0.37 (0.29, 0.48)
aluminum and magnesium hydroxide antacid | 20 mL single dose given 2 hours before raltegravir | 400 mg twice daily | 23 | 0.49 (0.33, 0.71) | 0.49 (0.35, 0.67) | 0.44 (0.34, 0.55)
aluminum and magnesium hydroxide antacid | 20 mL single dose given 2 hours after raltegravir | 400 mg twice daily | 23 | 0.78 (0.53, 1.13) | 0.70 (0.50, 0.96) | 0.43 (0.34, 0.55)
aluminum and magnesium hydroxide antacid | 20 mL single dose given 4 hours before raltegravir | 400 mg twice daily | 17 | 0.78 (0.55, 1.10) | 0.81 (0.63, 1.05) | 0.40 (0.31, 0.52)
aluminum and magnesium hydroxide antacid | 20 mL single dose given 4 hours after raltegravir | 400 mg twice daily | 18 | 0.70 (0.48, 1.04) | 0.68 (0.50, 0.92) | 0.38 (0.30, 0.49)
aluminum and magnesium hydroxide antacid | 20 mL single dose given 6 hours before raltegravir | 400 mg twice daily | 16 | 0.90 (0.58, 1.40) | 0.87 (0.64, 1.18) | 0.50 (0.39, 0.65)
aluminum and magnesium hydroxide antacid | 20 mL single dose given 6 hours after raltegravir | 400 mg twice daily | 16 | 0.90 (0.58, 1.41) | 0.89 (0.64, 1.22) | 0.51 (0.40, 0.64)
atazanavir | 400 mg daily | 100 mg single dose | 10 | 1.53 (1.11, 2.12) | 1.72 (1.47, 2.02) | 1.95 (1.30, 2.92)
atazanavir/ritonavir | 300 mg/100 mg daily | 400 mg twice daily | 10 | 1.24 (0.87, 1.77) | 1.41 (1.12, 1.78) | 1.77 (1.39, 2.25)
boceprevir | 800 mg three times daily | 400 mg single dose | 22 | 1.11 (0.91-1.36) | 1.04 (0.88-1.22) | 0.75 (0.45-1.23)
calcium carbonate antacid | 3000 mg single dose given with raltegravir | 400 mg twice daily | 24 | 0.48 (0.36, 0.63) | 0.45 (0.35, 0.57) | 0.68 (0.53, 0.87)
efavirenz | 600 mg daily | 400 mg single dose | 9 | 0.64 (0.41, 0.98) | 0.64 (0.52, 0.80) | 0.79 (0.49, 1.28)
etravirine | 200 mg twice daily | 400 mg twice daily | 19 | 0.89 (0.68, 1.15) | 0.90 (0.68, 1.18) | 0.66 (0.34, 1.26)
omeprazole | 20 mg daily | 400 mg single dose | 14 (10 for AUC) | 4.15 (2.82, 6.10) | 3.12 (2.13, 4.56) | 1.46 (1.10, 1.93)
rifampin | 600 mg daily | 400 mg single dose | 9 | 0.62 (0.37, 1.04) | 0.60 (0.39, 0.91) | 0.39 (0.30, 0.51)
rifampin | 600 mg daily | 400 mg twice daily when administered alone; 800 mg twice daily when administered with rifampin | 14 | 1.62 (1.12, 2.33) | 1.27 (0.94, 1.71) | 0.47 (0.36, 0.61)
ritonavir | 100 mg twice daily | 400 mg single dose | 10 | 0.76 (0.55, 1.04) | 0.84 (0.70, 1.01) | 0.99 (0.70, 1.40)
tenofovir | 300 mg daily | 400 mg twice daily | 9 | 1.64 (1.16, 2.32) | 1.49 (1.15, 1.94) | 1.03 (0.73, 1.45)
tipranavir/ritonavir | 500 mg/200 mg twice daily | 400 mg twice daily | 15 (14 for Cmin) | 0.82 (0.46, 1.46) | 0.76 (0.49, 1.19) | 0.45 (0.31, 0.66)

12.4 Microbiology

Mechanism of Action

Raltegravir inhibits the catalytic activity of HIV-1 integrase, an HIV-1 encoded enzyme that is required for viral replication. Inhibition of integrase prevents the covalent insertion, or integration, of unintegrated linear HIV-1 DNA into the host cell genome preventing the formation of the HIV-1 provirus. The provirus is required to direct the production of progeny virus, so inhibiting integration prevents propagation of the viral infection. Raltegravir did not significantly inhibit human phosphoryltransferases including DNA polymerases α, β, and γ.

Antiviral Activity in Cell Culture

Raltegravir at concentrations of 31 ± 20 nM resulted in 95% inhibition (EC95) of viral spread (relative to an untreated virus-infected culture) in human T-lymphoid cell cultures infected with the cell-line adapted HIV-1 variant H9IIIB. In addition, 5 clinical isolates of HIV-1 subtype B had EC95 values ranging from 9 to 19 nM in cultures of mitogen-activated human peripheral blood mononuclear cells. In a single-cycle infection assay, raltegravir inhibited infection of 23 HIV-1 isolates representing 5 non-B subtypes (A, C, D, F, and G) and 5 circulating recombinant forms (AE, AG, BF, BG, and cpx) with EC50 values ranging from 5 to 12 nM. Raltegravir also inhibited replication of an HIV-2 isolate when tested in CEMx174 cells (EC95 value = 6 nM). Additive to synergistic antiretroviral activity was observed when human T-lymphoid cells infected with the H9IIIB variant of HIV-1 were incubated with raltegravir in combination with non-nucleoside reverse transcriptase inhibitors (delavirdine, efavirenz, or nevirapine); nucleoside analog reverse transcriptase inhibitors (abacavir, didanosine, lamivudine, stavudine, tenofovir, or zidovudine); protease inhibitors (amprenavir, atazanavir, indinavir, lopinavir, nelfinavir, ritonavir, or saquinavir); or the entry inhibitor enfuvirtide.

Resistance

The mutations observed in the HIV-1 integrase coding sequence that contributed to raltegravir resistance (evolved either in cell culture or in subjects treated with raltegravir) generally included an amino acid substitution at either Y143 (changed to C, H, or R) or Q148 (changed to H, K, or R) or N155 (changed to H) plus one or more additional substitutions (i.e., L74M, E92Q, Q95K/R, T97A, E138A/K, G140A/S, V151I, G163R, H183P, Y226C/D/F/H, S230R, and D232N). E92Q and F121C are occasionally seen in the absence of substitutions at Y143, Q148, or N155 in raltegravir-treatment failure subjects.

Treatment-Naïve Adult Subjects: By Week 240 in the STARTMRK trial, the primary raltegravir resistance-associated substitutions were observed in 4 (2 with Y143H/R and 2 with Q148H/R) of the 12 virologic failure subjects with evaluable genotypic data from paired baseline and raltegravir treatment-failure isolates.

Treatment-Experienced Adult Subjects: By Week 96 in the BENCHMRK trials, at least one of the primary raltegravir resistance-associated substitutions, Y143C/H/R, Q148H/K/R, and N155H, was observed in 76 of the 112 virologic failure subjects with evaluable genotypic data from paired baseline and raltegravir treatment-failure isolates. The emergence of the primary raltegravir resistance-associated substitutions was observed cumulatively in 70 subjects by Week 48 and 78 subjects by Week 96, 15.2% and 17% of the raltegravir recipients, respectively. Some (n=58) of those HIV-1 isolates harboring one or more of the primary raltegravir resistance-associated substitutions were evaluated for raltegravir susceptibility yielding a median decrease of 26.3-fold (mean 48.9 ± 44.8-fold decrease, ranging from 0.8- to 159-fold) compared to the wild-type reference.

Cross Resistance

Cross resistance has been observed among HIV-1 integrase strand transfer inhibitors (INSTIs). Amino acid substitutions in HIV-1 integrase conferring resistance to raltegravir generally also confer resistance to elvitegravir. Substitutions at amino acid Y143 confer greater reductions in susceptibility to raltegravir than to elvitegravir, and the E92Q substitution confers greater reductions in susceptibility to elvitegravir than to raltegravir. Viruses harboring a substitution at amino acid Q148, along with one or more other raltegravir resistance substitutions, may also have clinically significant resistance to dolutegravir.

13 NONCLINICAL TOXICOLOGY

13.1 Carcinogenesis, Mutagenesis, Impairment of Fertility

Carcinogenicity studies of raltegravir in mice did not show any carcinogenic potential. At the highest dose levels, 400 mg/kg/day in females and 250 mg/kg/day in males, systemic exposure was 1.8-fold (females) or 1.2-fold (males) greater than the AUC (54 µM∙hr) at the 400-mg twice daily human dose. Treatment-related squamous cell carcinoma of nose/nasopharynx was observed in female rats dosed with 600 mg/kg/day raltegravir for 104 weeks. These tumors were possibly the result of local irritation and inflammation due to local deposition and/or aspiration of drug in the mucosa of the nose/nasopharynx during dosing. No tumors of the nose/nasopharynx were observed in rats dosed with 150 mg/kg/day (males) and 50 mg/kg/day (females) and the systemic exposure in rats was 1.7-fold (males) to 1.4-fold (females) greater than the AUC (54 μM∙hr) at the 400-mg twice daily human dose.

No evidence of mutagenicity or genotoxicity was observed in in vitro microbial mutagenesis (Ames) tests, in vitro alkaline elution assays for DNA breakage, and in vitro and in vivo chromosomal aberration studies.

No effect on fertility was seen in male and female rats at doses up to 600 mg/kg/day which resulted in a 3-fold exposure above the exposure at the recommended human dose.

14 CLINICAL STUDIES

Description of Clinical Studies

The evidence of durable efficacy of ISENTRESS is based on the analyses of 240-week data from a randomized, double-blind, active-control trial, STARTMRK (Protocol 021) in antiretroviral treatment-naïve HIV-1 infected adult subjects and 96-week data from 2 randomized, double-blind, placebo-controlled studies, BENCHMRK 1 and BENCHMRK 2 (Protocols 018 and 019), in antiretroviral treatment-experienced HIV-1 infected adult subjects.

14.1 Treatment-Naïve Adult Subjects

STARTMRK (Protocol 021) is a Phase 3 study to evaluate the safety and antiretroviral activity of ISENTRESS 400 mg twice daily + emtricitabine (+) tenofovir versus efavirenz 600 mg at bedtime plus emtricitabine (+) tenofovir in treatment-naïve HIV-1-infected subjects with HIV-1 RNA >5000 copies/mL. Randomization was stratified by screening HIV-1 RNA level (≤50,000 copies/mL; and >50,000 copies/mL) and by hepatitis status.

Table 11 shows the demographic characteristics of subjects in the group receiving ISENTRESS 400 mg twice daily and subjects in the comparator group.

Table 11: Baseline Characteristics
Randomized Study | ISENTRESS | Efavirenz
Protocol 021 | 400 mg Twice Daily | 600 mg At Bedtime
 | (N = 281) | (N = 282)
Gender
Male | 81% | 82%
Female | 19% | 18%
Race
White | 41% | 44%
Black | 12% | 8%
Asian | 13% | 11%
Hispanic | 21% | 24%
Native American | <1% | <1%
Multiracial | 12% | 13%
Region
Latin America | 35% | 34%
Southeast Asia | 12% | 10%
North America | 29% | 32%
EU/Australia | 23% | 23%
Age (years)
18-64 | 99% | 99%
≥65 | 1% | 1%
Mean (SD) | 38 (9) | 37 (10)
Median (min, max) | 37 (19 to 67) | 36 (19 to 71)
CD4+ Cell Count (cells/microL)
Mean (SD) | 219 (124) | 217 (134)
Median (min, max) | 212 (1 to 620) | 204 (4 to 807)
Plasma HIV-1 RNA (log10 copies/mL)
Mean (SD) | 5 (1) | 5 (1)
Median (min, max) | 5 (3 to 6) | 5 (4 to 6)
Plasma HIV-1 RNA (copies/mL)
Geometric Mean | 103205 | 106215
Median (min, max) | 114000 (400 to 750000) | 104000 (4410 to 750000)
History of AIDS [Includes additional subjects identified as having a history of AIDS.]
Yes | 19% | 21%
Viral Subtype
Clade B | 78% | 82%
Non-Clade B [Non-Clade B Subtypes (# of subjects): Clade A (4), A/C (1), A/G (2), A1 (1), AE (29), AG (12), BF (6), C (37), D (2), F (2), F1 (5), G (2), Complex (3).] | 21% | 17%
Baseline Plasma HIV-1 RNA
≤100,000 copies/mL | 45% | 49%
>100,000 copies/mL | 55% | 51%
Baseline CD4+ Cell Counts
≤50 cells/mm^3 | 10% | 11%
>50 cells/mm^3 and ≤200 cells/mm^3 | 37% | 37%
>200 cells/mm^3 | 53% | 51%
Hepatitis Status
Hepatitis B or C Positive [Evidence of hepatitis B surface antigen or evidence of HCV RNA by polymerase chain reaction (PCR) quantitative test for hepatitis C Virus.] | 6% | 6%
Notes:
ISENTRESS and Efavirenz were administered with emtricitabine (+) tenofovir
N = Number of subjects in each group.

Week 240 outcomes from Protocol 021 are shown in Table 12.

Table 12: Virologic Outcomes of Randomized Treatment of Protocol 021 at 240 Weeks
 | ISENTRESS 400 mg Twice Daily (N = 281) | Efavirenz 600 mg At Bedtime (N = 282) | Difference (ISENTRESS – Efavirenz) (CI)
Subjects with HIV-1 RNA less than 50 copies/mL | 66% | 60% | 6.6% (-1.4%, 14.5%)
Virologic Failure [Includes subjects who discontinued prior to Week 240 for lack of efficacy or subjects who are ≥50 copies/mL in the 240-week window (+/-6-weeks).] | 8% | 15%
No virologic data at Week 240 Window
Reasons
Discontinued study due to AE or death [Includes subjects who discontinued due to AE or Death at any time point from Day 1 through the Week 240 window if this resulted in no virologic data on treatment during Week 240 visit window.] | 5% | 10%
Discontinued study for other reasons [Other includes: withdrew consent, loss to follow-up, moved etc., if the viral load at the time of discontinuation was <50 copies/mL.] | 15% | 14%
Missing data during window but on study | 6% | 2%

The mean changes in CD4 count from baseline were 295 cells/mm^3 in the group receiving ISENTRESS 400 mg twice daily and 236 cells/mm^3 in the group receiving Efavirenz 600 mg at bedtime.

14.2 Treatment-Experienced Adult Subjects

BENCHMRK 1 and BENCHMRK 2 are Phase 3 studies to evaluate the safety and antiretroviral activity of ISENTRESS 400 mg twice daily in combination with an optimized background therapy (OBT), versus OBT alone, in HIV-1-infected subjects, 16 years or older, with documented resistance to at least 1 drug in each of 3 classes (NNRTIs, NRTIs, PIs) of antiretroviral therapies. Randomization was stratified by degree of resistance to PI (1PI vs. >1PI) and the use of enfuvirtide in the OBT. Prior to randomization, OBT was selected by the investigator based on genotypic/phenotypic resistance testing and prior ART history.

Table 13 shows the demographic characteristics of subjects in the group receiving ISENTRESS 400 mg twice daily and subjects in the placebo group.

Table 13: Baseline Characteristics
Randomized Studies Protocol 018 and 019 | ISENTRESS 400 mg Twice Daily + OBT | Placebo + OBT
Randomized Studies Protocol 018 and 019 | (N = 462) | (N = 237)
Randomized Studies Protocol 018 and 019 | Gender
Male | 88% | 89%
Female | 12% | 11%
Race
White | 65% | 73%
Black | 14% | 11%
Asian | 3% | 3%
Hispanic | 11% | 8%
Others | 6% | 5%
Age (years)
Median (min, max) | 45 (16 to 74) | 45 (17 to 70)
CD4+ Cell Count
Median (min, max), cells/mm^3 | 119 (1 to 792) | 123 (0 to 759)
≤50 cells/mm^3 | 32% | 33%
>50 and ≤200 cells/mm^3 | 37% | 36%
Plasma HIV-1 RNA
Median (min, max), log10 copies/mL | 4.8 (2 to 6) | 4.7 (2 to 6)
>100,000 copies/mL | 36% | 33%
History of AIDS
Yes | 92% | 91%
Prior Use of ART, Median (1st Quartile, 3rd Quartile)
Years of ART Use | 10 (7 to 12) | 10 (8 to 12)
Number of ART | 12 (9 to 15) | 12 (9 to 14)
Hepatitis Co-infection [Hepatitis B virus surface antigen positive or hepatitis C virus antibody positive.]
No Hepatitis B or C virus | 83% | 84%
Hepatitis B virus only | 8% | 3%
Hepatitis C virus only | 8% | 12%
Co-infection of Hepatitis B and C virus | 1% | 1%
Stratum
Enfuvirtide in OBT | 38% | 38%
Resistant to ≥2 PI | 97% | 95%

Table 14 compares the characteristics of optimized background therapy at baseline in the group receiving ISENTRESS 400 mg twice daily and subjects in the control group.

Table 14: Characteristics of Optimized Background Therapy at Baseline
Randomized Studies Protocol 018 and 019 | ISENTRESS 400 mg Twice Daily + OBT | Placebo + OBT
 | (N = 462) | (N = 237)
Number of ARTs in OBT
Median (min, max) | 4 (1 to 7) | 4 (2 to 7)
Number of Active PI in OBT by Phenotypic Resistance Test [Darunavir use in OBT in darunavir-naïve subjects was counted as one active PI.]
0 | 36% | 41%
1 or more | 60% | 58%
Phenotypic Sensitivity Score (PSS) [The Phenotypic Sensitivity Score (PSS) and the Genotypic Sensitivity Score (GSS) were defined as the total oral ARTs in OBT to which a subject's viral isolate showed phenotypic sensitivity and genotypic sensitivity, respectively, based upon phenotypic and genotypic resistance tests. Enfuvirtide use in OBT in enfuvirtide-naïve subjects was counted as one active drug in OBT in the GSS and PSS. Similarly, darunavir use in OBT in darunavir-naïve subjects was counted as one active drug in OBT.]
0 | 15% | 18%
1 | 31% | 30%
2 | 31% | 28%
3 or more | 18% | 20%
Genotypic Sensitivity Score (GSS)
0 | 25% | 27%
1 | 38% | 40%
2 | 24% | 21%
3 or more | 11% | 10%

Week 96 outcomes for the 699 subjects randomized and treated with the recommended dose of ISENTRESS 400 mg twice daily or placebo in the pooled BENCHMRK 1 and 2 studies are shown in Table 15.

Table 15: Virologic Outcomes of Randomized Treatment of Protocols 018 and 019 at 96 Weeks (Pooled Analysis)
 | ISENTRESS 400 mg Twice Daily + OBT (N = 462) | Placebo + OBT (N = 237)
Subjects with HIV-1 RNA less than 50 copies/mL | 55% | 27%
Virologic Failure [Includes subjects who switched to open-label raltegravir after Week 16 due to the protocol-defined virologic failure, subjects who discontinued prior to Week 96 for lack of efficacy, subjects changed OBT due to lack of efficacy prior to Week 96, or subjects who were ≥50 copies in the 96 week window.] | 35% | 66%
No virologic data at Week 96 Window
Reasons
Discontinued study due to AE or death [Includes subjects who discontinued due to AE or Death at any time point from Day 1 through the Week 96 window if this resulted in no virologic data on treatment during the Week 96 window.] | 3% | 3%
Discontinued study for other reasons [Other includes: withdrew consent, loss to follow-up, moved etc., if the viral load at the time of discontinuation was <50 copies/mL.] | 4% | 4%
Missing data during window but on study | 4% | <1%

The mean changes in CD4 count from baseline were 118 cells/mm^3 in the group receiving ISENTRESS 400 mg twice daily and 47 cells/mm^3 for the control group.

Treatment-emergent CDC Category C events occurred in 4% of the group receiving ISENTRESS 400 mg twice daily and 5% of the control group.

Virologic responses at Week 96 by baseline genotypic and phenotypic sensitivity score are shown in Table 16.

Table 16: Virologic Response at 96 Week Window by Baseline Genotypic/Phenotypic Sensitivity Score
 | Percent with HIV-1 RNA <50 copies/mL At Week 96
 | n | ISENTRESS 400 mg Twice Daily + OBT (N = 462) | n | Placebo + OBT (N = 237)
Phenotypic Sensitivity Score (PSS) [The Phenotypic Sensitivity Score (PSS) and the Genotypic Sensitivity Score (GSS) were defined as the total oral ARTs in OBT to which a subject's viral isolate showed phenotypic sensitivity and genotypic sensitivity, respectively, based upon phenotypic and genotypic resistance tests. Enfuvirtide use in OBT in enfuvirtide-naïve subjects was counted as one active drug in OBT in the GSS and PSS. Similarly, darunavir use in OBT in darunavir-naïve subjects was counted as one active drug in OBT.]
0 | 67 | 43 | 43 | 5
1 | 144 | 58 | 71 | 23
2 | 142 | 61 | 66 | 32
3 or more | 85 | 48 | 48 | 42
Genotypic Sensitivity Score (GSS)
0 | 116 | 39 | 65 | 5
1 | 177 | 62 | 95 | 26
2 | 111 | 61 | 49 | 53
3 or more | 51 | 49 | 23 | 35

Switch of Suppressed Subjects from Lopinavir (+) Ritonavir to Raltegravir

The SWITCHMRK 1 & 2 Phase 3 studies evaluated HIV-1 infected subjects receiving suppressive therapy (HIV-1 RNA <50 copies/mL on a stable regimen of lopinavir 200 mg (+) ritonavir 50 mg 2 tablets twice daily plus at least 2 nucleoside reverse transcriptase inhibitors for >3 months) and randomized them 1:1 to either continue lopinavir (+) ritonavir (n=174 and n=178, SWITCHMRK 1 & 2, respectively) or replace lopinavir (+) ritonavir with ISENTRESS 400 mg twice daily (n=174 and n=176, respectively). The primary virology endpoint was the proportion of subjects with HIV-1 RNA less than 50 copies/mL at Week 24 with a prespecified non-inferiority margin of -12% for each study; and the frequency of adverse events up to 24 weeks.

Subjects with a prior history of virological failure were not excluded and the number of previous antiretroviral therapies was not limited.

These studies were terminated after the primary efficacy analysis at Week 24 because they each failed to demonstrate non-inferiority of switching to ISENTRESS versus continuing on lopinavir (+) ritonavir. In the combined analysis of these studies at Week 24, suppression of HIV-1 RNA to less than 50 copies/mL was maintained in 82.3% of the ISENTRESS group versus 90.3% of the lopinavir (+) ritonavir group. Clinical and laboratory adverse events occurred at similar frequencies in the treatment groups.

14.3 Pediatric Subjects

2 to 18 Years of Age

IMPAACT P1066 is a Phase I/II open label multicenter trial to evaluate the pharmacokinetic profile, safety, tolerability, and efficacy of raltegravir in HIV infected children. This study enrolled 126 treatment experienced children and adolescents 2 to 18 years of age. Subjects were stratified by age, enrolling adolescents first and then successively younger children. Subjects were enrolled into cohorts according to age and received the following formulations: Cohort I (12 to less than 18 years old), 400 mg film-coated tablet; Cohort IIa (6 to less than 12 years old), 400 mg film-coated tablet; Cohort IIb (6 to less than 12 years old), chewable tablet; Cohort III (2 to less than 6 years), chewable tablet. Raltegravir was administered with an optimized background regimen.

The initial dose finding stage included intensive pharmacokinetic evaluation. Dose selection was based upon achieving similar raltegravir plasma exposure and trough concentration as seen in adults, and acceptable short term safety. After dose selection, additional subjects were enrolled for evaluation of long term safety, tolerability and efficacy. Of the 126 subjects, 96 received the recommended dose of ISENTRESS [see Dosage and Administration (2.3)] .

These 96 subjects had a median age of 13 (range 2 to 18) years, were 51% Female, 34% Caucasian, and 59% Black. At baseline, mean plasma HIV-1 RNA was 4.3 log10 copies/mL, median CD4 cell count was 481 cells/mm^3 (range: 0 – 2361) and median CD4% was 23.3% (range: 0 – 44). Overall, 8% had baseline plasma HIV-1 RNA >100,000 copies/mL and 59% had a CDC HIV clinical classification of category B or C. Most subjects had previously used at least one NNRTI (78%) or one PI (83%).

Ninety-three (97%) subjects 2 to 18 years of age completed 24 weeks of treatment (3 discontinued due to non-compliance). At Week 24, 54% achieved HIV RNA <50 copies/mL; 66% achieved HIV RNA <400 copies/mL. The mean CD4 count (percent) increase from baseline to Week 24 was 119 cells/mm^3 (3.8%).

4 Weeks to Less Than 2 Years of Age

IMPAACT P1066 also enrolled HIV-infected, infants and toddlers 4 weeks to less than 2 years of age (Cohorts IV and V) who had received prior antiretroviral therapy either as prophylaxis for prevention of mother-to-child transmission (PMTCT) and/or as combination antiretroviral therapy for treatment of HIV infection. Raltegravir was administered as an oral suspension without regard to food in combination with an optimized background regimen.

The 26 subjects had a median age of 28 weeks (range: 4 -100), were 35% female, 85% Black and 8% Caucasian. At baseline, mean plasma HIV-1 RNA was 5.7 log10 copies/mL (range: 3.1 – 7), median CD4 cell count was 1400 cells/mm^3 (range: 131 – 3648) and median CD4% was 18.6% (range: 3.3 – 39.3). Overall, 69% had baseline plasma HIV-1 RNA exceeding 100,000 copies/mL and 23% had a CDC HIV clinical classification of category B or C. None of the 26 patients were completely treatment naïve. All infants under 6 months of age had received nevirapine or zidovudine for prevention of mother-to-infant transmission, and 43% of patients greater than 6 months of age had received two or more antiretrovirals.

Of the 26 treated subjects, 23 subjects were included in the Week 24 and 48 efficacy analyses, respectively. All 26 treated subjects were included for safety analyses.

At Week 24, 39% achieved HIV RNA <50 copies/mL and 61% achieved HIV RNA <400 copies/mL. The mean CD4 count (percent) increase from baseline to Week 24 was 500 cells/mm^3 (7.5%).

At Week 48, 44% achieved HIV RNA <50 copies/mL and 61% achieved HIV RNA <400 copies/mL. The mean CD4 count (percent) increase from baseline to Week 48 was 492 cells/mm^3 (7.8%).

16 HOW SUPPLIED/STORAGE AND HANDLING

ISENTRESS tablets 400 mg are pink, oval-shaped, film-coated tablets with "227" on one side. They are supplied as follows:

- NDC 68071-2113-6 bottles of 6

Storage and Handling

400 mg Film-coated Tablets, Chewable Tablets and For Oral Suspension

Store at 20-25°C (68-77°F); excursions permitted to 15-30°C (59-86°F). See USP Controlled Room Temperature.

Chewable Tablets

Store in the original package with the bottle tightly closed. Keep the desiccant in the bottle to protect from moisture.

For Oral Suspension

Store in the original container. Do not open foil packet until ready for use.

17 PATIENT COUNSELING INFORMATION

Advise patients to read the FDA-approved patient labeling (Patient Information and Instructions for Use).

General Information

Instruct patients to reread patient labeling each time the prescription is renewed.

Patients should remain under the care of a physician when using ISENTRESS. Instruct patients to inform their physician or pharmacist if they develop any unusual symptom, or if any known symptom persists or worsens.

ISENTRESS is not a cure for HIV-1 infection and patients may continue to experience illnesses associated with HIV-1 infection such as opportunistic infections. Tell patients that sustained decreases in plasma HIV RNA have been associated with a reduced risk of progression to AIDS and death. Patients should remain on continuous HIV therapy to control HIV infection and decrease HIV-related illnesses.

Advise patients to avoid doing things that can spread HIV-1 infection to others.

- Do not share needles or other injection equipment.
- Do not share personal items that can have blood or body fluids on them, like toothbrushes and razor blades.
- Do not have any kind of sex without protection. Always practice safe sex by using a latex or polyurethane condom to lower the chance of sexual contact with semen, vaginal secretions, or blood.
- Do not breastfeed. Mothers with HIV-1 should not breastfeed because HIV-1 can be passed to the baby in the breast milk. Also, it is unknown if ISENTRESS can be passed to the baby through breast milk and whether it could harm the baby.

General Dosing Instructions

Instruct patients that if they miss a dose of ISENTRESS, they should take it as soon as they remember. If they do not remember until it is time for the next dose, instruct them to skip the missed dose and go back to the regular schedule. Instruct patients not to double their next dose or take more than the prescribed dose.

Film-Coated Tablets and Chewable Tablets

Inform patients that the chewable tablet forms can be chewed or swallowed whole, but the film-coated tablets must be swallowed whole.

For Oral Suspension

Instruct parents and/or caregivers to read the Instructions for Use before preparing and administering ISENTRESS for oral suspension to pediatric patients. Instruct parents and/or caregivers that ISENTRESS for oral suspension should be administered within 30 minutes of mixing.

Severe and Potentially Life-threatening Rash

Inform patients that severe and potentially life-threatening rash has been reported. Advise patients to immediately contact their healthcare provider if they develop rash. Instruct patients to immediately stop taking ISENTRESS and other suspect agents, and seek medical attention if they develop a rash associated with any of the following symptoms as it may be a sign of a more serious reaction such as Stevens-Johnson syndrome, toxic epidermal necrolysis or severe hypersensitivity: fever, generally ill feeling, extreme tiredness, muscle or joint aches, blisters, oral lesions, eye inflammation, facial swelling, swelling of the eyes, lips, mouth, breathing difficulty, and/or signs and symptoms of liver problems (e.g., yellowing of the skin or whites of the eyes, dark or tea colored urine, pale colored stools/bowel movements, nausea, vomiting, loss of appetite, or pain, aching or sensitivity on the right side below the ribs). Inform patients that if severe rash occurs, their physician will closely monitor them, order laboratory tests and initiate appropriate therapy.

Rhabdomyolysis

Before patients begin ISENTRESS, ask them if they have a history of rhabdomyolysis, myopathy or increased creatine kinase or if they are taking medications known to cause these conditions such as statins, fenofibrate, gemfibrozil or zidovudine.

Instruct patients to immediately report to their healthcare provider any unexplained muscle pain, tenderness, or weakness while taking ISENTRESS.

Phenylketonuria

Alert patients with phenylketonuria that ISENTRESS Chewable Tablets contain phenylalanine [see Warnings and Precautions (5.3)].

Drug Interactions

Instruct patients to avoid taking aluminum and/or magnesium containing antacids during treatment with ISENTRESS [see Drug Interactions (7.2)] .

Distributed by:
Merck Sharp & Dohme Corp., a subsidiary of Merck & Co., Inc.
Whitehouse Station, NJ 08889, USA

For patent information: www.merck.com/product/patent/home.html

Copyright © 2014 Merck Sharp & Dohme Corp., a subsidiary of Merck & Co., Inc.
All rights reserved.

uspi-mk0518-mf-1502r030

Patient Information

ISENTRESS® (eye sen tris)
(raltegravir)
film-coated tablets
ISENTRESS® (eye sen tris)
(raltegravir)
chewable tablets
ISENTRESS® (eye sen tris)
(raltegravir)
for oral suspension

Read this Patient Information before you start taking ISENTRESS and each time you get a refill. There may be new information. This information does not take the place of talking with your doctor about your medical condition or your treatment.

What is ISENTRESS?

ISENTRESS is a prescription HIV medicine used with other antiretroviral medicines to treat Human Immunodeficiency Virus-1 (HIV-1) infection in people 4 weeks of age and older. HIV is the virus that causes AIDS (Acquired Immune Deficiency Syndrome).

It is not known if ISENTRESS is safe and effective in babies under 4 weeks of age.

When used with other HIV medicines to treat HIV-1 infection, ISENTRESS may help:

- reduce the amount of HIV in your blood. This is called "viral load".
- increase the number of white blood cells called CD4+ (T) cells in your blood, which help fight off other infections.
- reduce the amount of HIV-1 and increase the CD4+ (T) cells in your blood, which may help improve your immune system. This may reduce your risk of death or getting infections that can happen when your immune system is weak (opportunistic infections).

ISENTRESS does not cure HIV-1 infection or AIDS.

You must stay on continuous HIV therapy to control HIV-1 infection and decrease HIV-related illnesses.

Avoid doing things that can spread HIV-1 infection to others.

- Do not share or re-use needles or other injection equipment.
- Do not share personal items that can have blood or body fluids on them, like toothbrushes and razor blades.
- Do not have any kind of sex without protection. Always practice safe sex by using a latex or polyurethane condom to lower the chance of sexual contact with any body fluids such as semen, vaginal secretions, or blood.

Ask your doctor if you have any questions on how to prevent passing HIV to other people.

What should I tell my doctor before taking ISENTRESS?

Before you take ISENTRESS, tell your doctor if you:

- have liver problems
- have a history of a muscle disorder called rhabdomyolysis or myopathy
- have increased levels of creatine kinase in your blood
- have phenylketonuria (PKU). ISENTRESS chewable tablets contain phenylalanine as part of the artificial sweetener, aspartame. The artificial sweetener may be harmful to people with PKU.
- have any other medical conditions
- are pregnant or plan to become pregnant. It is not known if ISENTRESS can harm your unborn baby.
  Pregnancy Registry: There is a pregnancy registry for women who take antiviral medicines during pregnancy. The purpose of this registry is to collect information about the health of you and your baby. Talk to your doctor about how you can take part in this registry.
- are breastfeeding or plan to breastfeed. Do not breastfeed if you take ISENTRESS.
  - You should not breastfeed if you have HIV-1 because of the risk of passing HIV-1 to your baby.
  - Talk with your doctor about the best way to feed your baby.

Tell your doctor about all the medicines you take, including, prescription and over-the-counter medicines, vitamins, and herbal supplements. Some medicines interact with ISENTRESS. Keep a list of your medicines to show your doctor and pharmacist.

- You can ask your doctor or pharmacist for a list of medicines that interact with ISENTRESS.
- Do not start taking a new medicine without telling your healthcare provider. Your healthcare provider can tell you if it is safe to take ISENTRESS with other medicines.

How should I take ISENTRESS?

- Take ISENTRESS exactly as prescribed by your doctor.
- Do not change your dose of ISENTRESS or stop your treatment without talking with your doctor first.
- Stay under the care of your doctor while taking ISENTRESS.
- ISENTRESS film-coated tablets must be swallowed whole.
- ISENTRESS chewable tablets may be chewed or swallowed whole.
- ISENTRESS for oral suspension should be given to your child within 30 minutes of mixing. See the detailed Instructions for Use that comes with ISENTRESS for oral suspension , for information about the correct way to mix and give a dose of ISENTRESS for oral suspension. If you have questions about how to mix or give ISENTRESS for oral suspension, talk to your doctor or pharmacist.
- Do not switch between the film-coated tablet, the chewable tablet, or the oral suspension without talking with your doctor first.
- Do not run out of ISENTRESS. Get a refill of your ISENTRESS from your doctor or pharmacy before you run out.
- If you miss a dose, take it as soon as you remember. If you do not remember until it is time for your next dose, skip the missed dose and go back to your regular schedule. Do not double your next dose or take more ISENTRESS than prescribed.
- If you take too much ISENTRESS, call your doctor or go to the nearest hospital emergency room right away.

What are the possible side effects of ISENTRESS?

ISENTRESS can cause serious side effects including:

- Serious skin reactions and allergic reactions. Some people who take ISENTRESS develop serious skin reactions and allergic reactions that can be severe, and may be life-threatening or lead to death. If you develop a rash with any of the following symptoms, stop using ISENTRESS and call your doctor right away:
  - fever
  - generally ill feeling
  - extreme tiredness
  - muscle or joint aches
  - blisters or sores in mouth
  - blisters or peeling of the skin
  - redness or swelling of the eyes
  - swelling of the mouth or face
  - problems breathing

Sometimes allergic reactions can affect body organs, such as your liver. Call your doctor right away if you have any of the following signs or symptoms of liver problems:

-
  - yellowing of your skin or whites of your eyes
  - dark or tea colored urine
  - pale colored stools (bowel movements)
  - nausea or vomiting
  - loss of appetite
  - pain, aching, or tenderness on the right side of your stomach area

- Changes in your immune system (Immune Reconstitution Syndrome) can happen when you start taking HIV-1 medicines. Your immune system may get stronger and begin to fight infections that have been hidden in your body for a long time. Tell your doctor right away if you start having new symptoms after starting your HIV-1 medicine.

The most common side effects of ISENTRESS include:

- trouble sleeping
- headache
- dizziness
- nausea
- tiredness

Less common side effects of ISENTRESS include:

- depression
- hepatitis
- genital herpes
- herpes zoster including shingles
- kidney failure
- kidney stones
- indigestion or stomach area pain
- vomiting
- suicidal thoughts and actions
- weakness

Tell your doctor right away if you get unexplained muscle pain, tenderness, or weakness while taking ISENTRESS. These may be signs of a rare serious muscle problem that can lead to kidney problems.

Tell your doctor if you have any side effect that bothers you or that does not go away.

These are not all the possible side effects of ISENTRESS. For more information, ask your doctor or pharmacist.

Call your doctor for medical advice about side effects. You may report side effects to FDA at 1-800-FDA-1088.

How should I store ISENTRESS?

Film-Coated Tablets:

- Store ISENTRESS film-coated tablets at room temperature between 68°F to 77°F (20°C to 25°C).

Chewable Tablets:

- Store ISENTRESS chewable tablets at room temperature between 68°F to 77°F (20°C to 25°C).
- Store ISENTRESS chewable tablets in the original package with the bottle tightly closed.
- Keep the drying agent (desiccant) in the bottle to protect from moisture.

For Oral Suspension:

- Store ISENTRESS for oral suspension at room temperature between 68°F to 77°F (20°C to 25°C).
- Store in the original container. Do not open the foil packet until ready for use.

Keep ISENTRESS and all medicines out of the reach of children.

General information about ISENTRESS

Medicines are sometimes prescribed for purposes other than those listed in a Patient Information Leaflet. Do not use ISENTRESS for a condition for which it was not prescribed. Do not give ISENTRESS to other people, even if they have the same symptoms you have. It may harm them.

You can ask your doctor or pharmacist for information about ISENTRESS that is written for health professionals.

For more information go to www.ISENTRESS.com or call 1-800-622-4477.

What are the ingredients in ISENTRESS?

ISENTRESS film-coated tablets:

Active ingredient: raltegravir

Inactive ingredients: calcium phosphate dibasic anhydrous, hypromellose 2208, lactose monohydrate, magnesium stearate, microcrystalline cellulose, poloxamer 407 (contains 0.01% butylated hydroxytoluene as antioxidant), sodium stearyl fumarate.

The film coating contains: black iron oxide, polyethylene glycol 3350, polyvinyl alcohol, red iron oxide, talc and titanium dioxide.

ISENTRESS chewable tablets:

Active ingredient: raltegravir

Inactive ingredients: ammonium hydroxide, crospovidone, ethylcellulose 20 cP, fructose, hydroxypropyl cellulose, hypromellose 2910/6cP, magnesium stearate, mannitol, medium chain triglycerides, monoammonium glycyrrhizinate, natural and artificial flavors (orange, banana, and masking that contains aspartame), oleic acid, PEG 400, saccharin sodium, sodium citrate dihydrate, sodium stearyl fumarate, sorbitol, sucralose and yellow iron oxide. The 100 mg chewable tablet also contains red iron oxide.

ISENTRESS for oral suspension:

Active ingredient: raltegravir

Inactive ingredients: ammonium hydroxide, banana with other natural flavors, carboxymethylcellulose sodium, crospovidone, ethylcellulose 20 cP, fructose, hydroxypropyl cellulose, hypromellose 2910/6cP, macrogol/PEG 400, magnesium stearate, maltodextrin, mannitol, medium chain triglycerides, microcrystalline cellulose, monoammonium glycyrrhizinate, oleic acid, sorbitol, sucralose and sucrose.

This Patient Information has been approved by the U.S. Food and Drug Administration.

Distributed by:
Merck Sharp & Dohme Corp., a subsidiary of Merck & Co., Inc.
Whitehouse Station, NJ 08889, USA

Revised February 2015

For patent information: www.merck.com/product/patent/home.html

Copyright © 2007, 2013 Merck Sharp & Dohme Corp., a subsidiary of Merck & Co., Inc.
All rights reserved.

usppi-mk0518-mf-1502r026

Instructions for Use

ISENTRESS® (eye sen tris)
(raltegravir)
for oral suspension

Read this Instructions for Use before you mix and give a dose of ISENTRESS for oral suspension to your child for the first time, and each time you get a refill. There may be new information. These instructions will help you to correctly mix and give a dose of ISENTRESS for oral suspension to your child.

See the Patient Information leaflet that comes with ISENTRESS for oral suspension for more information about ISENTRESS.

Your doctor will decide the right dose based on your child's weight.

Ask your doctor or pharmacist if you have any questions about how to mix or give ISENTRESS for oral suspension to your child.

Each ISENTRESS for oral suspension kit contains the following supplies (see Figure A):

- 2 reusable mixing cups with attached lids
- 2 reusable 5 mL dosing syringes
- 60 foil packets containing ISENTRESS for oral suspension

For each dose of ISENTRESS for oral suspension you will need the following:

- 1 mixing cup with attached lid
- 1 dosing syringe (5mL)
- 1 foil packet containing the medicine
- Drinking water (not included in kit)

How do I prepare a dose of ISENTRESS for oral suspension?

Step 1. Fill mixing cup about half-way with drinking water (see Figure B).

Step 2. Fill the dosing syringe. Start with the plunger pushed all the way inside the barrel of the syringe. Insert the tip of the syringe into the water and pull back on the plunger to the 5 mL marking on the barrel of the syringe (see Figure C).

Step 3. Pour out remaining water from mixing cup (see Figure D).

Step 4. Add the 5 mL of water from the dosing syringe back into the mixing cup by pressing down on the plunger (see Figure E).

Step 5. Open 1 foil packet. There is a notch that you can use to tear open the foil packet, or you may use scissors to cut along the dotted line. Pour entire contents into mixing cup (see Figure F).

Step 6. Close the attached lid to seal the mixing cup (see Figure G). It will snap shut.

Step 7. Swirl the mixing cup to mix using a gentle circular motion for 30-60 seconds (see Figure H). Do not turn the mixing cup upside down. The liquid will be cloudy.

Step 8. Open the mixing cup. Put the tip of the syringe into the liquid and pull back the plunger to the mL marking that matches your child's prescribed dose (see Figure I). Your child's dose may be different from the one shown in the figure.

How should I give a dose of ISENTRESS for oral suspension?

Step 9. Place the tip of the dosing syringe in your child's mouth and turn it toward either cheek. Gently push down on the plunger to give the medicine (see Figure J). Give the dose of ISENTRESS oral suspension to your child within 30 minutes of mixing. If you are not able to give your child's dose within 30 minutes of mixing, pour the unused medicine into the trash. You will need to mix a new dose.

How should I dispose of leftover ISENTRESS for oral suspension?

Step 10. Pour any leftover medicine from the mixing cup into the trash (see Figure K).

Step 11. Remove plunger from the barrel of the dosing syringe. Hand wash the dosing syringe and mixing cup with warm water and dish soap. Rinse with water and air dry (see Figure L).

How should I store ISENTRESS for oral suspension?

- Store ISENTRESS for oral suspension at room temperature between 68°F to 77°F (20°C to 25°C).
- Store in the original container. Do not open the foil packets until ready for use.

Keep ISENTRESS for oral suspension and all medicines out of the reach of children.

For more information go to www.ISENTRESS.com or call 1-800-622-4477.

This Instructions for Use has been approved by the U.S. Food and Drug Administration.

Distributed by:
Merck Sharp & Dohme Corp., a subsidiary of Merck & Co., Inc.
Whitehouse Station, NJ 08889, USA

Issued December 2013

For patent information: www.merck.com/product/patent/home.html

Copyright © 2013 Merck Sharp & Dohme Corp., a subsidiary of Merck & Co., Inc.
All rights reserved.

ifu-mk0518-mf-1312r000